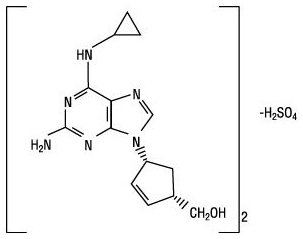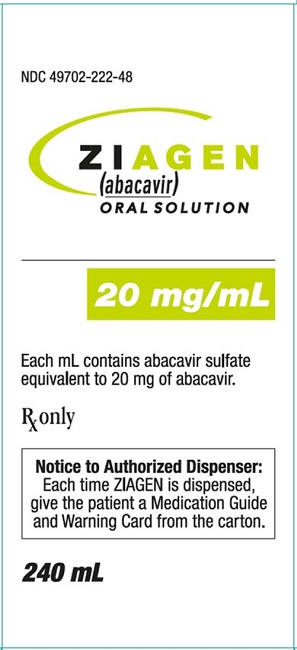 DRUG LABEL: ZIAGEN
NDC: 49702-222 | Form: SOLUTION
Manufacturer: ViiV Healthcare Company
Category: prescription | Type: HUMAN PRESCRIPTION DRUG LABEL
Date: 20230929

ACTIVE INGREDIENTS: ABACAVIR SULFATE 20 mg/1 mL
INACTIVE INGREDIENTS: ANHYDROUS CITRIC ACID; METHYLPARABEN; PROPYLPARABEN; PROPYLENE GLYCOL; SACCHARIN SODIUM; TRISODIUM CITRATE DIHYDRATE; SORBITOL; WATER

HIGHLIGHTS OF PRESCRIBING INFORMATION

These highlights do not include all the information needed to use ZIAGEN safely and effectively. See full prescribing information for ZIAGEN.
ZIAGEN (abacavir) tablets, for oral use
ZIAGEN (abacavir) oral solution
Initial U.S. Approval: 1998

WARNING: HYPERSENSITIVITY REACTIONS

See full prescribing information for complete boxed warning.

- Serious and sometimes fatal hypersensitivity reactions have occurred with ZIAGEN (abacavir). (5.1)
- Hypersensitivity to ZIAGEN is a multi-organ clinical syndrome. (5.1)
- Patients who carry the HLA-B*5701 allele are at a higher risk of experiencing a hypersensitivity reaction to abacavir. (5.1)
- ZIAGEN is contraindicated in patients with a prior hypersensitivity reaction to abacavir and in HLA-B*5701-positive patients. (4)
- Discontinue ZIAGEN as soon as a hypersensitivity reaction is suspected. Regardless of HLA-B*5701 status, permanently discontinue ZIAGEN if hypersensitivity cannot be ruled out, even when other diagnoses are possible. (5.1)
- Following a hypersensitivity reaction to ZIAGEN, NEVER restart ZIAGEN or any other abacavir-containing product. (5.1)

1 INDICATIONS AND USAGE

ZIAGEN, a nucleoside analogue human immunodeficiency virus (HIV-1) reverse transcriptase inhibitor, is indicated in combination with other antiretroviral agents for the treatment of HIV-1 infection. (1)

2 DOSAGE AND ADMINISTRATION

- Before initiating ZIAGEN, screen for the HLA-B*5701 allele. (2.1)
- Adults: 600 mg daily, administered as either 300 mg twice daily or 600 mg once daily. (2.2)
- Pediatric Patients Aged 3 Months and Older: Administered either once or twice daily. Dose should be calculated on body weight (kg) and should not exceed 600 mg daily. (2.3)
- Patients with Hepatic Impairment: Mild hepatic impairment – 200 mg twice daily. (2.4)

3 DOSAGE FORMS AND STRENGTHS

- Tablets: 300 mg scored (3)
- Oral Solution: 20 mg per mL (3)

4 CONTRAINDICATIONS

- Presence of HLA-B*5701 allele. (4)
- Prior hypersensitivity reaction to abacavir. (4)
- Moderate or severe hepatic impairment. (4)

5 WARNINGS AND PRECAUTIONS

- Lactic acidosis and severe hepatomegaly with steatosis, including fatal cases, have been reported with the use of nucleoside analogues. (5.2)
- Immune reconstitution syndrome has been reported in patients treated with combination antiretroviral therapy. (5.3)

6 ADVERSE REACTIONS

- The most commonly reported adverse reactions of at least moderate intensity (incidence greater than or equal to 10%) in adult HIV-1 clinical trials were nausea, headache, malaise and fatigue, nausea and vomiting, and dreams/sleep disorders. (6.1)
- The most commonly reported adverse reactions of at least moderate intensity (incidence greater than or equal to 5%) in pediatric HIV-1 clinical trials were fever and/or chills, nausea and vomiting, skin rashes, and ear/nose/throat infections. (6.2)
To report SUSPECTED ADVERSE REACTIONS, contact ViiV Healthcare at 1-877-844-8872 or FDA at 1-800-FDA-1088 or www.fda.gov/medwatch.

7 DRUG INTERACTIONS

- Methadone: An increased methadone dose may be required in a small number of patients. (7.1)
- Riociguat: The riociguat dose may need to be reduced. (7.2)

8 USE IN SPECIFIC POPULATIONS

- Lactation: Women infected with HIV should be instructed not to breastfeed due to potential for HIV transmission. (8.2)

FULL PRESCRIBING INFORMATION

WARNING: HYPERSENSITIVITY REACTIONS

Serious and sometimes fatal hypersensitivity reactions, with multiple organ involvement, have occurred with ZIAGEN (abacavir).

Patients who carry the HLA‑B*5701 allele are at a higher risk of a hypersensitivity reaction to abacavir; although, hypersensitivity reactions have occurred in patients who do not carry the HLA‑B*5701 allele [see Warnings and Precautions (5.1)].

ZIAGEN is contraindicated in patients with a prior hypersensitivity reaction to abacavir and in HLA‑B*5701-positive patients [see Contraindications (4), Warnings and Precautions (5.1)]. All patients should be screened for the HLA‑B*5701 allele prior to initiating therapy with ZIAGEN or reinitiation of therapy with ZIAGEN, unless patients have a previously documented HLA‑B*5701 allele assessment. Discontinue ZIAGEN immediately if a hypersensitivity reaction is suspected, regardless of HLA-B*5701 status and even when other diagnoses are possible [see Contraindications (4), Warnings and Precautions (5.1)].

Following a hypersensitivity reaction to ZIAGEN, NEVER restart ZIAGEN or any other abacavir-containing product because more severe symptoms, including death can occur within hours. Similar severe reactions have also occurred rarely following the reintroduction of abacavir-containing products in patients who have no history of abacavir hypersensitivity [see Warnings and Precautions (5.1)].

1 INDICATIONS AND USAGE

ZIAGEN tablets and oral solution, in combination with other antiretroviral agents, are indicated for the treatment of human immunodeficiency virus (HIV-1) infection.

2 DOSAGE AND ADMINISTRATION

2.1 Screening for HLA-B*5701 Allele prior to Starting ZIAGEN

Screen for the HLA‑B*5701 allele prior to initiating therapy with ZIAGEN [see Boxed Warning, Warnings and Precautions (5.1)].

2.2 Recommended Dosage for Adult Patients

The recommended dosage of ZIAGEN for adults is 600 mg daily, administered orally as either 300 mg twice daily or 600 mg once daily, in combination with other antiretroviral agents.

2.3 Recommended Dosage for Pediatric Patients

The recommended dosage of ZIAGEN oral solution in HIV-1–infected pediatric patients aged 3 months and older is 8 mg per kg orally twice daily or 16 mg per kg orally once daily (up to a maximum of 600 mg daily) in combination with other antiretroviral agents.

ZIAGEN is also available as a scored tablet for HIV-1–infected pediatric patients weighing greater than or equal to 14 kg for whom a solid dosage form is appropriate. Before prescribing ZIAGEN tablets, children should be assessed for the ability to swallow tablets. If a child is unable to reliably swallow ZIAGEN tablets, the oral solution formulation should be prescribed. The recommended oral dosage of ZIAGEN tablets for HIV-1–infected pediatric patients is presented in Table 1.

Table 1. Dosing Recommendations for ZIAGEN Scored Tablets in Pediatric Patients
Weight; (kg) | Once-Daily Dosing Regimena | Twice-Daily Dosing Regimen
Weight; (kg) | Once-Daily Dosing Regimena | AM Dose | PM Dose | Total Daily Dose
14 to <20 | 1 tablet (300 mg) | ½ tablet (150 mg) | ½ tablet (150 mg) | 300 mg
≥20 to <25 | 1½ tablets (450 mg) | ½ tablet (150 mg) | 1 tablet (300 mg) | 450 mg
≥25 | 2 tablets (600 mg) | 1 tablet (300 mg) | 1 tablet (300 mg) | 600 mg
a Data regarding the efficacy of once-daily dosing is limited to subjects who transitioned from twice-daily dosing to once-daily dosing after 36 weeks of treatment [see Clinical Studies (14.2)].

2.4 Recommended Dosage for Patients with Hepatic Impairment

The recommended dose of ZIAGEN in patients with mild hepatic impairment (Child‑Pugh Class A) is 200 mg twice daily. To enable dose reduction, ZIAGEN oral solution (10 mL twice daily) should be used for the treatment of these patients. The safety, efficacy, and pharmacokinetic properties of abacavir have not been established in patients with moderate to severe hepatic impairment; therefore, ZIAGEN is contraindicated in these patients.

3 DOSAGE FORMS AND STRENGTHS

ZIAGEN tablets contain 300 mg of abacavir as abacavir sulfate. The tablets are yellow, biconvex, scored, capsule-shaped, film-coated, and imprinted with “GX 623” on both sides.

ZIAGEN oral solution contains 20 mg per mL of abacavir as abacavir sulfate. The solution is a clear to opalescent, yellowish, strawberry-banana-flavored liquid, which may turn brown over time.

4 CONTRAINDICATIONS

ZIAGEN is contraindicated in patients:

- who have the HLA‑B*5701 allele [see Warnings and Precautions (5.1)].
- with prior hypersensitivity reaction to abacavir [see Warnings and Precautions (5.1)].
- with moderate or severe hepatic impairment [see Use in Specific Populations (8.6)].

5 WARNINGS AND PRECAUTIONS

5.1 Hypersensitivity Reactions

Serious and sometimes fatal hypersensitivity reactions have occurred with ZIAGEN (abacavir). These hypersensitivity reactions have included multi-organ failure and anaphylaxis and typically occurred within the first 6 weeks of treatment with ZIAGEN (median time to onset was 9 days); although abacavir hypersensitivity reactions have occurred any time during treatment [see Adverse Reactions (6.1)]. Patients who carry the HLA-B*5701 allele are at a higher risk of abacavir hypersensitivity reactions; although, patients who do not carry the HLA‑B*5701 allele have developed hypersensitivity reactions. Hypersensitivity to abacavir was reported in approximately 206 (8%) of 2,670 patients in 9 clinical trials with abacavir-containing products where HLA‑B*5701 screening was not performed. The incidence of suspected abacavir hypersensitivity reactions in clinical trials was 1% when subjects carrying the HLA‑B*5701 allele were excluded. In any patient treated with abacavir, the clinical diagnosis of hypersensitivity reaction must remain the basis of clinical decision making.

Due to the potential for severe, serious, and possibly fatal hypersensitivity reactions with ZIAGEN:

- All patients should be screened for the HLA‑B*5701 allele prior to initiating therapy with ZIAGEN or reinitiation of therapy with ZIAGEN, unless patients have a previously documented HLA‑B*5701 allele assessment.
- ZIAGEN is contraindicated in patients with a prior hypersensitivity reaction to abacavir and in HLA‑B*5701-positive patients.
- Before starting ZIAGEN, review medical history for prior exposure to any abacavir-containing product. NEVER restart ZIAGEN or any other abacavir‑containing product following a hypersensitivity reaction to abacavir, regardless of HLA‑B*5701 status.
- To reduce the risk of a life-threatening hypersensitivity reaction, regardless of HLA-B*5701 status, discontinue ZIAGEN immediately if a hypersensitivity reaction is suspected, even when other diagnoses are possible (e.g., acute onset respiratory diseases such as pneumonia, bronchitis, pharyngitis, or influenza; gastroenteritis; or reactions to other medications).
- If a hypersensitivity reaction cannot be ruled out, do not restart ZIAGEN or any other abacavir-containing products because more severe symptoms which may include life-threatening hypotension and death, can occur within hours.
- If a hypersensitivity reaction is ruled out, patients may restart ZIAGEN. Rarely, patients who have stopped abacavir for reasons other than symptoms of hypersensitivity have also experienced life-threatening reactions within hours of reinitiating abacavir therapy. Therefore, reintroduction of ZIAGEN or any other abacavir-containing product is recommended only if medical care can be readily accessed.
- A Medication Guide and Warning Card that provide information about recognition of hypersensitivity reactions should be dispensed with each new prescription and refill.

5.2 Lactic Acidosis and Severe Hepatomegaly with Steatosis

Lactic acidosis and severe hepatomegaly with steatosis, including fatal cases, have been reported with the use of nucleoside analogues, including ZIAGEN. A majority of these cases have been in women. Female sex and obesity may be risk factors for the development of lactic acidosis and severe hepatomegaly with steatosis in patients treated with antiretroviral nucleoside analogues. Treatment with ZIAGEN should be suspended in any patient who develops clinical or laboratory findings suggestive of lactic acidosis or pronounced hepatotoxicity, which may include hepatomegaly and steatosis even in the absence of marked transaminase elevations.

5.3 Immune Reconstitution Syndrome

Immune reconstitution syndrome has been reported in patients treated with combination antiretroviral therapy, including ZIAGEN. During the initial phase of combination antiretroviral treatment, patients whose immune systems respond may develop an inflammatory response to indolent or residual opportunistic infections (such as Mycobacterium avium infection, cytomegalovirus, Pneumocystis jirovecii pneumonia [PCP], or tuberculosis), which may necessitate further evaluation and treatment.

Autoimmune disorders (such as Graves’ disease, polymyositis, and Guillain-Barré syndrome) have also been reported to occur in the setting of immune reconstitution; however, the time to onset is more variable and can occur many months after initiation of treatment.

5.4 Myocardial Infarction

Several prospective, observational, epidemiological studies have reported an association with the use of abacavir and the risk of myocardial infarction (MI). Meta-analyses of randomized, controlled, clinical trials have observed no excess risk of MI in abacavir-treated subjects as compared with control subjects. To date, there is no established biological mechanism to explain a potential increase in risk. In totality, the available data from the observational studies and from controlled clinical trials show inconsistency; therefore, evidence for a causal relationship between abacavir treatment and the risk of MI is inconclusive.

As a precaution, the underlying risk of coronary heart disease should be considered when prescribing antiretroviral therapies, including abacavir, and action taken to minimize all modifiable risk factors (e.g., hypertension, hyperlipidemia, diabetes mellitus, smoking).

6 ADVERSE REACTIONS

The following adverse reactions are discussed in other sections of the labeling:

- Serious and sometimes fatal hypersensitivity reactions [see Boxed Warning, Warnings and Precautions (5.1)].
- Lactic acidosis and severe hepatomegaly with steatosis [see Warnings and Precautions (5.2)].
- Immune reconstitution syndrome [see Warnings and Precautions (5.3)].
- Myocardial infarction [see Warnings and Precautions (5.4)].

6.1 Clinical Trials Experience in Adult Subjects

Because clinical trials are conducted under widely varying conditions, adverse reaction rates observed in the clinical trials of a drug cannot be directly compared with rates in the clinical trials of another drug and may not reflect the rates observed in clinical practice.

Serious and Fatal Abacavir-Associated Hypersensitivity Reactions

In clinical trials, serious and sometimes fatal hypersensitivity reactions have occurred with abacavir [see Boxed Warning, Warnings and Precautions (5.1)]. These reactions have been characterized by 2 or more of the following signs or symptoms: (1) fever; (2) rash; (3) gastrointestinal symptoms (including nausea, vomiting, diarrhea, or abdominal pain); (4) constitutional symptoms (including generalized malaise, fatigue, or achiness); (5) respiratory symptoms (including dyspnea, cough, or pharyngitis). Almost all abacavir hypersensitivity reactions include fever and/or rash as part of the syndrome.

Other signs and symptoms have included lethargy, headache, myalgia, edema, arthralgia, and paresthesia. Anaphylaxis, liver failure, renal failure, hypotension, adult respiratory distress syndrome, respiratory failure, myolysis, and death have occurred in association with these hypersensitivity reactions. Physical findings have included lymphadenopathy, mucous membrane lesions (conjunctivitis and mouth ulcerations), and maculopapular or urticarial rash (although some patients had other types of rashes and others did not have a rash). There were reports of erythema multiforme. Laboratory abnormalities included elevated liver chemistries, elevated creatine phosphokinase, elevated creatinine, and lymphopenia, and abnormal chest x-ray findings (predominantly infiltrates, which were localized).

Additional Adverse Reactions with Use of ZIAGEN

Therapy-Naive Adults: Treatment-emergent clinical adverse reactions (rated by the investigator as moderate or severe) with a greater than or equal to 5% frequency during therapy with ZIAGEN 300 mg twice daily, lamivudine 150 mg twice daily, and efavirenz 600 mg daily compared with zidovudine 300 mg twice daily, lamivudine 150 mg twice daily, and efavirenz 600 mg daily from CNA30024 are listed in Table 2.

Table 2. Treatment-Emergent (All Causality) Adverse Reactions of at Least Moderate Intensity (Grades 2-4, Greater than or Equal to 5% Frequency) in Therapy-Naive Adults (CNA30024a) through 48 Weeks of Treatment
Adverse Reaction | ZIAGEN plus Lamivudine plus Efavirenz; (n = 324) | Zidovudine plus Lamivudine plus Efavirenz; (n = 325)
Dreams/sleep disorders | 10% | 10%
Drug hypersensitivity | 9% | <1%b
Headaches/migraine | 7% | 11%
Nausea | 7% | 11%
Fatigue/malaise | 7% | 10%
Diarrhea | 7% | 6%
Rashes | 6% | 12%
Abdominal pain/gastritis/ gastrointestinal signs and symptoms | 6% | 8%
Depressive disorders | 6% | 6%
Dizziness | 6% | 6%
Musculoskeletal pain | 6% | 5%
Bronchitis | 4% | 5%
Vomiting | 2% | 9%
a This trial used double-blind ascertainment of suspected hypersensitivity reactions. During the blinded portion of the trial, suspected hypersensitivity to abacavir was reported by investigators in 9% of 324 subjects in the abacavir group and 3% of 325 subjects in the zidovudine group.
b Ten (3%) cases of suspected drug hypersensitivity were reclassified as not being due to abacavir following unblinding.

Treatment-emergent clinical adverse reactions (rated by the investigator as moderate or severe) with a greater than or equal to 5% frequency during therapy with ZIAGEN 300 mg twice daily, lamivudine 150 mg twice daily, and zidovudine 300 mg twice daily compared with indinavir 800 mg 3 times daily, lamivudine 150 mg twice daily, and zidovudine 300 mg twice daily from CNA3005 are listed in Table 3.

Table 3. Treatment-Emergent (All Causality) Adverse Reactions of at Least Moderate Intensity (Grades 2-4, Greater than or Equal to 5% Frequency) in Therapy-Naive Adults (CNA3005) through 48 Weeks of Treatment
Adverse Reaction | ZIAGEN plus Lamivudine/Zidovudine; (n = 262) | Indinavir plus Lamivudine/Zidovudine; (n = 264)
Nausea | 19% | 17%
Headache | 13% | 9%
Malaise and fatigue | 12% | 12%
Nausea and vomiting | 10% | 10%
Hypersensitivity reaction | 8% | 2%
Diarrhea | 7% | 5%
Fever and/or chills | 6% | 3%
Depressive disorders | 6% | 4%
Musculoskeletal pain | 5% | 7%
Skin rashes | 5% | 4%
Ear/nose/throat infections | 5% | 4%
Viral respiratory infections | 5% | 5%
Anxiety | 5% | 3%
Renal signs/symptoms | <1% | 5%
Pain (non-site-specific) | <1% | 5%

Five subjects receiving ZIAGEN in CNA3005 experienced worsening of pre-existing depression compared with none in the indinavir arm. The background rates of pre-existing depression were similar in the 2 treatment arms.

ZIAGEN Once Daily versus ZIAGEN Twice Daily (CNA30021): Treatment-emergent clinical adverse reactions (rated by the investigator as at least moderate) with a greater than or equal to 5% frequency during therapy with ZIAGEN 600 mg once daily or ZIAGEN 300 mg twice daily, both in combination with lamivudine 300 mg once daily and efavirenz 600 mg once daily from CNA30021, were similar. For hypersensitivity reactions, subjects receiving ZIAGEN once daily showed a rate of 9% in comparison with a rate of 7% for subjects receiving ZIAGEN twice daily. However, subjects receiving ZIAGEN 600 mg once daily experienced a significantly higher incidence of severe drug hypersensitivity reactions and severe diarrhea compared with subjects who received ZIAGEN 300 mg twice daily. Five percent (5%) of subjects receiving ZIAGEN 600 mg once daily had severe drug hypersensitivity reactions compared with 2% of subjects receiving ZIAGEN 300 mg twice daily. Two percent (2%) of subjects receiving ZIAGEN 600 mg once daily had severe diarrhea while none of the subjects receiving ZIAGEN 300 mg twice daily had this event.

Laboratory Abnormalities: Laboratory abnormalities (Grades 3-4) in therapy-naive adults during therapy with ZIAGEN 300 mg twice daily, lamivudine 150 mg twice daily, and efavirenz 600 mg daily compared with zidovudine 300 mg twice daily, lamivudine 150 mg twice daily, and efavirenz 600 mg daily from CNA30024 are listed in Table 4.

Table 4. Laboratory Abnormalities (Grades 3-4) in Therapy-Naive Adults (CNA30024) through 48 Weeks of Treatment
Grade 3/4; Laboratory Abnormalities | ZIAGEN plus; Lamivudine plus Efavirenz; (n = 324) | Zidovudine plus; Lamivudine plus Efavirenz (n = 325)
Elevated CPK (>4 X ULN) | 8% | 8%
Elevated ALT (>5 X ULN) | 6% | 6%
Elevated AST (>5 X ULN) | 6% | 5%
Hypertriglyceridemia (>750 mg/dL) | 6% | 5%
Hyperamylasemia (>2 X ULN) | 4% | 5%
Neutropenia (ANC <750/mm^3) | 2% | 4%
Anemia (Hgb ≤6.9 gm/dL) | <1% | 2%
Thrombocytopenia (Platelets <50,000/mm^3) | 1% | <1%
Leukopenia (WBC ≤1,500/mm^3) | <1% | 2%
ULN = Upper limit of normal.
n = Number of subjects assessed.

Laboratory abnormalities in CNA3005 are listed in Table 5.

Table 5. Treatment-Emergent Laboratory Abnormalities (Grades 3-4) in CNA3005
Grade 3/4; Laboratory Abnormalities | ZIAGEN plus Lamivudine/Zidovudine; (n = 262) | Indinavir plus Lamivudine/Zidovudine; (n = 264)
Elevated CPK (>4 x ULN) | 18 (7%) | 18 (7%)
ALT (>5.0 x ULN) | 16 (6%) | 16 (6%)
Neutropenia (<750/mm^3) | 13 (5%) | 13 (5%)
Hypertriglyceridemia (>750 mg/dL) | 5 (2%) | 3 (1%)
Hyperamylasemia (>2.0 x ULN) | 5 (2%) | 1 (<1%)
Hyperglycemia (>13.9 mmol/L) | 2 (<1%) | 2 (<1%)
Anemia (Hgb ≤6.9 g/dL) | 0 (0%) | 3 (1%)
ULN = Upper limit of normal.
n = Number of subjects assessed.

The frequencies of treatment-emergent laboratory abnormalities were comparable between treatment groups in CNA30021.

6.2 Clinical Trials Experience in Pediatric Subjects

Therapy-Experienced Pediatric Subjects (Twice-Daily Dosing)

Treatment-emergent clinical adverse reactions (rated by the investigator as moderate or severe) with a greater than or equal to 5% frequency during therapy with ZIAGEN 8 mg per kg twice daily, lamivudine 4 mg per kg twice daily, and zidovudine 180 mg per m^2 twice daily compared with lamivudine 4 mg per kg twice daily and zidovudine 180 mg per m^2 twice daily from CNA3006 are listed in Table 6.

Table 6. Treatment-Emergent (All Causality) Adverse Reactions of at Least Moderate Intensity (Grades 2-4, Greater than or Equal to 5% Frequency) in Therapy-Experienced Pediatric Subjects (CNA3006) through 16 Weeks of Treatment
Adverse Reaction | ZIAGEN plus Lamivudine plus Zidovudine; (n = 102) | Lamivudine plus Zidovudine; (n = 103)
Fever and/or chills | 9% | 7%
Nausea and vomiting | 9% | 2%
Skin rashes | 7% | 1%
Ear/nose/throat infections | 5% | 1%
Pneumonia | 4% | 5%
Headache | 1% | 5%

Laboratory Abnormalities: In CNA3006, laboratory abnormalities (anemia, neutropenia, liver function test abnormalities, and CPK elevations) were observed with similar frequencies as in a trial of therapy-naive adults (CNA30024). Mild elevations of blood glucose were more frequent in pediatric subjects receiving ZIAGEN (CNA3006) as compared with adult subjects (CNA30024).

Other Adverse Events

In addition to adverse reactions and laboratory abnormalities reported in Tables 2, 3, 4, 5, and 6, other adverse reactions observed in the expanded access program were pancreatitis and increased GGT.

Pediatric Subjects Once-Daily versus Twice-Daily Dosing (COL105677): The safety of once-daily compared with twice-daily dosing of ZIAGEN was assessed in the ARROW trial. Primary safety assessment in the ARROW trial was based on Grade 3 and Grade 4 adverse events. The frequency of Grade 3 and 4 adverse events was similar among subjects randomized to once-daily dosing compared with subjects randomized to twice-daily dosing. One event of Grade 4 hepatitis in the once-daily cohort was considered as uncertain causality by the investigator and all other Grade 3 or 4 adverse events were considered not related by the investigator.

6.3 Postmarketing Experience

The following adverse reactions have been identified during postmarketing use of ZIAGEN. Because these reactions are reported voluntarily from a population of unknown size, it is not always possible to reliably estimate their frequency or establish a causal relationship to drug exposures.

Body as a Whole

Redistribution/accumulation of body fat.

Cardiovascular

Myocardial infarction.

Hepatic

Lactic acidosis and hepatic steatosis [see Warnings and Precautions (5.2)].

Skin

Suspected Stevens-Johnson syndrome (SJS) and toxic epidermal necrolysis (TEN) have been reported in patients receiving abacavir primarily in combination with medications known to be associated with SJS and TEN, respectively. Because of the overlap of clinical signs and symptoms between hypersensitivity to abacavir and SJS and TEN, and the possibility of multiple drug sensitivities in some patients, abacavir should be discontinued and not restarted in such cases.

There have also been reports of erythema multiforme with abacavir use [see Adverse Reactions (6.1)].

7 DRUG INTERACTIONS

7.1 Methadone

In a trial of 11 HIV‑1–infected subjects receiving methadone‑maintenance therapy with 600 mg of ZIAGEN twice daily (twice the currently recommended dose), oral methadone clearance increased [see Clinical Pharmacology (12.3)]. This alteration will not result in a methadone dose modification in the majority of patients; however, an increased methadone dose may be required in a small number of patients.

7.2 Riociguat

Coadministration with fixed-dose abacavir/dolutegravir/lamivudine resulted in increased riociguat exposure, which may increase the risk of riociguat adverse reactions [see Clinical Pharmacology (12.3)]. The riociguat dose may need to be reduced. See full prescribing information for ADEMPAS (riociguat).

8 USE IN SPECIFIC POPULATIONS

8.1 Pregnancy

Pregnancy Exposure Registry

There is a pregnancy exposure registry that monitors pregnancy outcomes in women exposed to ZIAGEN during pregnancy. Healthcare Providers are encouraged to register patients by calling the Antiretroviral Pregnancy Registry (APR) at 1-800-258-4263.

Risk Summary

Available data from the APR show no difference in the overall risk of birth defects for abacavir compared with the background rate for birth defects of 2.7% in the Metropolitan Atlanta Congenital Defects Program (MACDP) reference population (see Data). The APR uses the MACDP as the U.S. reference population for birth defects in the general population. The MACDP evaluates women and infants from a limited geographic area and does not include outcomes for births that occurred at less than 20 weeks’ gestation. The rate of miscarriage is not reported in the APR. The estimated background rate of miscarriage in clinically recognized pregnancies in the U.S. general population is 15% to 20%. The background risk for major birth defects and miscarriage for the indicated population is unknown.

In animal reproduction studies, oral administration of abacavir to pregnant rats during organogenesis resulted in fetal malformations and other embryonic and fetal toxicities at exposures 35 times the human exposure (AUC) at the recommended clinical daily dose. However, no adverse developmental effects were observed following oral administration of abacavir to pregnant rabbits during organogenesis, at exposures approximately 9 times the human exposure (AUC) at the recommended clinical dose (see Data).

Data

Human Data: Based on prospective reports to the APR of exposures to abacavir during pregnancy resulting in live births (including over 1,300 exposed in the first trimester and over 1,300 exposed in the second/third trimester), there was no difference between the overall risk of birth defects for abacavir compared with the background birth defect rate of 2.7% in the U.S. reference population of the MACDP. The prevalence of defects in live births was 3.2% (95% CI: 2.3% to 4.3%) following first trimester exposure to abacavir-containing regimens and 2.9% (95% CI: 2.1% to 4.0%) following second/third trimester exposure to abacavir-containing regimens.

Abacavir has been shown to cross the placenta and concentrations in neonatal plasma at birth were essentially equal to those in maternal plasma at delivery [see Clinical Pharmacology (12.3)].

Animal Data: Abacavir was administered orally to pregnant rats (at 100, 300, and 1,000 mg per kg per day) and rabbits (at 125, 350, or 700 mg per kg per day) during organogenesis (on Gestation Days 6 through 17 and 6 through 20, respectively). Fetal malformations (increased incidences of fetal anasarca and skeletal malformations) or developmental toxicity (decreased fetal body weight and crown‑rump length) were observed in rats at doses up to 1,000 mg per kg per day, resulting in exposures approximately 35 times the human exposure (AUC) at the recommended daily dose. No developmental effects were observed in rats at 100 mg per kg per day, resulting in exposures (AUC) 3.5 times the human exposure at the recommended daily dose. In a fertility and early embryo-fetal development study conducted in rats (at 60, 160, or 500 mg per kg per day), embryonic and fetal toxicities (increased resorptions, decreased fetal body weights) or toxicities to the offspring (increased incidence of stillbirth and lower body weights) occurred at doses up to 500 mg per kg per day. No developmental effects were observed in rats at 60 mg per kg per day, resulting in exposures (AUC) approximately 4 times the human exposure at the recommended daily dose. Studies in pregnant rats showed that abacavir is transferred to the fetus through the placenta. In pregnant rabbits, no developmental toxicities and no increases in fetal malformations occurred at up to the highest dose evaluated, resulting in exposures (AUC) approximately 9 times the human exposure at the recommended dose.

8.2 Lactation

Risk Summary

The Centers for Disease Control and Prevention recommends that HIV‑1–infected mothers in the U.S. not breastfeed their infants to avoid risking postnatal transmission of HIV‑1 infection. Abacavir is present in human milk. There is no information on the effects of abacavir on the breastfed infant or the effects of the drug on milk production. Because of the potential for (1) HIV‑1 transmission (in HIV-negative infants), (2) developing viral resistance (in HIV-positive infants), and (3) adverse reactions in a breastfed infant, instruct mothers not to breastfeed if they are receiving ZIAGEN.

8.4 Pediatric Use

The safety and effectiveness of ZIAGEN have been established in pediatric patients aged 3 months and older. Use of ZIAGEN is supported by pharmacokinetic trials and evidence from adequate and well-controlled trials of ZIAGEN in adults and pediatric subjects [see Dosage and Administration (2.3), Adverse Reactions (6.2), Clinical Pharmacology (12.3), Clinical Studies (14.2)].

8.5 Geriatric Use

Clinical trials of ZIAGEN did not include sufficient numbers of subjects aged 65 and over to determine whether they respond differently from younger subjects. In general, caution should be exercised in the administration of ZIAGEN in elderly patients reflecting the greater frequency of decreased hepatic, renal, or cardiac function, and of concomitant disease or other drug therapy.

8.6 Patients with Impaired Hepatic Function

A dose reduction is required for patients with mild hepatic impairment (Child-Pugh Class A) [see Dosage and Administration (2.4)]. The safety, efficacy, and pharmacokinetic properties of abacavir have not been established in patients with moderate or severe hepatic impairment; therefore, ZIAGEN is contraindicated in these patients [see Contraindications (4), Clinical Pharmacology (12.3)].

10 OVERDOSAGE

There is no known specific treatment for overdose with ZIAGEN. If overdose occurs, the patient should be monitored and standard supportive treatment applied as required. It is not known whether abacavir can be removed by peritoneal dialysis or hemodialysis.

11 DESCRIPTION

ZIAGEN is the brand name for abacavir sulfate, a synthetic carbocyclic nucleoside analogue with inhibitory activity against HIV-1. The chemical name of abacavir sulfate is (1S,cis)-4-[2-amino-6-(cyclopropylamino)-9H-purin-9-yl]-2-cyclopentene-1-methanol sulfate (salt) (2:1). Abacavir sulfate is the enantiomer with 1S, 4R absolute configuration on the cyclopentene ring. It has a molecular formula of (C14H18N6O)2•H2SO4 and a molecular weight of 670.76 g per mol. It has the following structural formula:

Abacavir sulfate is a white to off-white solid and is soluble in water.

ZIAGEN tablets are for oral administration. Each tablet contains abacavir sulfate equivalent to 300 mg of abacavir as active ingredient and the following inactive ingredients: colloidal silicon dioxide, magnesium stearate, microcrystalline cellulose, and sodium starch glycolate. The tablets are coated with a film that is made of hypromellose, polysorbate 80, synthetic yellow iron oxide, titanium dioxide, and triacetin.

ZIAGEN oral solution is for oral administration. Each milliliter (1 mL) of ZIAGEN oral solution contains abacavir sulfate equivalent to 20 mg of abacavir (i.e., 20 mg per mL) as active ingredient and the following inactive ingredients: artificial strawberry and banana flavors, citric acid (anhydrous), methylparaben and propylparaben (added as preservatives), propylene glycol, saccharin sodium, sodium citrate (dihydrate), sorbitol solution, and water.

In vivo, abacavir sulfate dissociates to its free base, abacavir. Dosages are expressed in terms of abacavir.

12 CLINICAL PHARMACOLOGY

12.1 Mechanism of Action

Abacavir is an antiretroviral agent [see Microbiology (12.4)].

12.3 Pharmacokinetics

Pharmacokinetics in Adults

The pharmacokinetic properties of abacavir were independent of dose over the range of 300 to 1,200 mg per day.

Absorption: Following oral administration, abacavir is rapidly absorbed and extensively distributed. The geometric mean absolute bioavailability of the tablet was 83%. Plasma abacavir AUC was similar following administration of the oral solution or tablets. After oral administration of 300 mg twice daily in 20 subjects, the steady-state peak serum abacavir concentration (Cmax) was 3.0 ± 0.89 mcg per mL (mean ± SD) and AUC(0-12 h) was 6.02 ± 1.73 mcg•hour per mL. After oral administration of a single dose of 600 mg of abacavir in 20 subjects, Cmax was 4.26 ± 1.19 mcg per mL (mean ± SD) and AUC∞ was 11.95 ± 2.51 mcg•hour per mL.

Effect of Food: Bioavailability of abacavir tablets was assessed in the fasting and fed states with no significant difference in systemic exposure (AUC∞); therefore, ZIAGEN tablets may be administered with or without food. Systemic exposure to abacavir was comparable after administration of ZIAGEN oral solution and ZIAGEN tablets. Therefore, these products may be used interchangeably.

Distribution: The apparent volume of distribution after IV administration of abacavir was 0.86 ± 0.15 L per kg, suggesting that abacavir distributes into extravascular space. In 3 subjects, the CSF AUC(0-6 h) to plasma abacavir AUC(0-6 h) ratio ranged from 27% to 33%.

Binding of abacavir to human plasma proteins is approximately 50% and was independent of concentration. Total blood and plasma drug-related radioactivity concentrations are identical, demonstrating that abacavir readily distributes into erythrocytes.

Elimination: In single-dose trials, the observed elimination half-life (t½) was 1.54 ± 0.63 hours. After intravenous administration, total clearance was 0.80 ± 0.24 L per hour per kg (mean ± SD).

Metabolism: In humans, abacavir is not significantly metabolized by cytochrome P450 enzymes. The primary routes of elimination of abacavir are metabolism by alcohol dehydrogenase to form the 5′-carboxylic acid and glucuronyl transferase to form the 5′-glucuronide. The metabolites do not have antiviral activity. In vitro experiments reveal that abacavir does not inhibit human CYP3A4, CYP2D6, or CYP2C9 activity at clinically relevant concentrations.

Excretion: Elimination of abacavir was quantified in a mass balance trial following administration of a 600-mg dose of ^14C-abacavir: 99% of the radioactivity was recovered, 1.2% was excreted in the urine as abacavir, 30% as the 5′-carboxylic acid metabolite, 36% as the 5′-glucuronide metabolite, and 15% as unidentified minor metabolites in the urine. Fecal elimination accounted for 16% of the dose.

Specific Populations

Patients with Renal Impairment: The pharmacokinetic properties of ZIAGEN have not been determined in patients with impaired renal function. Renal excretion of unchanged abacavir is a minor route of elimination in humans.

Patients with Hepatic Impairment: The pharmacokinetics of abacavir have been studied in subjects with mild hepatic impairment (Child-Pugh Class A). Results showed that there was a mean increase of 89% in the abacavir AUC and an increase of 58% in the half-life of abacavir after a single dose of 600 mg of abacavir. The AUCs of the metabolites were not modified by mild liver disease; however, the rates of formation and elimination of the metabolites were decreased [see Contraindications (4), Use in Specific Populations (8.6)].

Pregnant Women: Abacavir pharmacokinetics were studied in 25 pregnant women during the last trimester of pregnancy receiving abacavir 300 mg twice daily. Abacavir exposure (AUC) during pregnancy was similar to those in postpartum and in HIV-infected non-pregnant historical controls. Consistent with passive diffusion of abacavir across the placenta, abacavir concentrations in neonatal plasma cord samples at birth were essentially equal to those in maternal plasma at delivery.

Pediatric Patients: The pharmacokinetics of abacavir have been studied after either single or repeat doses of ZIAGEN in 169 pediatric subjects. Subjects receiving abacavir oral solution according to the recommended dosage regimen achieved plasma concentrations of abacavir similar to adults. Subjects receiving abacavir oral tablets achieved higher plasma concentrations of abacavir than subjects receiving oral solution.

The pharmacokinetics of abacavir dosed once daily in HIV‑1–infected pediatric subjects aged 3 months through 12 years was evaluated in 3 trials (PENTA 13 [n = 14], PENTA 15 [n = 18], and ARROW [n = 36]). All 3 trials were 2-period, crossover, open-label pharmacokinetic trials of twice- versus once-daily dosing of abacavir and lamivudine. For the oral solution as well as the tablet formulation, these 3 trials demonstrated that once-daily dosing provides comparable AUC0-24 to twice-daily dosing of abacavir at the same total daily dose. The mean Cmax was approximately 1.6- to 2.3-fold higher with abacavir once-daily dosing compared with twice-daily dosing.

Geriatric Patients: The pharmacokinetics of ZIAGEN have not been studied in subjects older than 65 years.

Male and Female Patients: A population pharmacokinetic analysis in HIV-1–infected male (n = 304) and female (n = 67) subjects showed no gender differences in abacavir AUC normalized for lean body weight.

Racial Groups: There are no significant or clinically relevant racial differences between blacks and whites in abacavir pharmacokinetics.

Drug Interaction Studies

Effect of Abacavir on the Pharmacokinetics of Other Agents: In vitro studies have shown that abacavir has potential to inhibit CYP1A1 and limited potential to inhibit metabolism mediated by CYP3A4. Abacavir did not inhibit or induce other CYP enzymes (such as CYP2C9 or CYP2D6).

Based on in vitro study results, abacavir at therapeutic drug exposures is not expected to affect the pharmacokinetics of drugs that are substrates of the following transporters: organic anion transporter polypeptide (OATP)1B1/3, breast cancer resistance protein (BCRP) or P-glycoprotein (P-gp), organic cation transporter (OCT)1, OCT2, or multidrug and toxic extrusion protein (MATE)1 and MATE2-K.

Riociguat: Coadministration of a single dose of riociguat (0.5 mg) to HIV-1–infected subjects receiving fixed-dose abacavir/dolutegravir/lamivudine is reported to increase riociguat AUC(∞) compared with riociguat AUC(∞) reported in healthy subjects due to CYP1A1 inhibition by abacavir. The exact magnitude of increase in riociguat exposure has not been fully characterized based on findings from two studies [see Drug Interactions (7.2)].

Effect of Other Agents on the Pharmacokinetics of Abacavir: In vitro, abacavir is not a substrate of OATP1B1, OAP1B3, OCT1, OCT2, OAT1, MATE1, MATE2-K, multidrug resistance-associated protein (MRP)2 or MRP4; therefore, drugs that modulate these transporters are not expected to affect abacavir plasma concentrations. Abacavir is a substrate of BCRP and P-gp in vitro; however, considering its absolute bioavailability (83%), modulators of these transporters are unlikely to result in a clinically relevant impact on abacavir concentrations.

Lamivudine and/or Zidovudine: Fifteen HIV-1–infected subjects were enrolled in a crossover-designed drug interaction trial evaluating single doses of abacavir (600 mg), lamivudine (150 mg), and zidovudine (300 mg) alone or in combination. Analysis showed no clinically relevant changes in the pharmacokinetics of abacavir with the addition of lamivudine or zidovudine or the combination of lamivudine and zidovudine. Lamivudine exposure (AUC decreased 15%) and zidovudine exposure (AUC increased 10%) did not show clinically relevant changes with concurrent abacavir.

Ethanol: Abacavir has no effect on the pharmacokinetic properties of ethanol. Ethanol decreases the elimination of abacavir causing an increase in overall exposure. Due to the common metabolic pathways of abacavir and ethanol via alcohol dehydrogenase, the pharmacokinetic interaction between abacavir and ethanol was studied in 24 HIV‑1–infected male subjects. Each subject received the following treatments on separate occasions: a single 600‑mg dose of abacavir, 0.7 g per kg ethanol (equivalent to 5 alcoholic drinks), and abacavir 600 mg plus 0.7 g per kg ethanol. Coadministration of ethanol and abacavir resulted in a 41% increase in abacavir AUC∞ and a 26% increase in abacavir t½. Abacavir had no effect on the pharmacokinetic properties of ethanol, so no clinically significant interaction is expected in men. This interaction has not been studied in females.

Methadone: In a trial of 11 HIV‑1–infected subjects receiving methadone‑maintenance therapy (40 mg and 90 mg daily), with 600 mg of ZIAGEN twice daily (twice the currently recommended dose), oral methadone clearance increased 22% (90% CI: 6% to 42%). This alteration will not result in a methadone dose modification in the majority of patients; however, an increased methadone dose may be required in a small number of patients [see Drug Interactions (7.1)]. The addition of methadone had no clinically significant effect on the pharmacokinetic properties of abacavir.

12.4 Microbiology

Abacavir is a carbocyclic synthetic nucleoside analogue. Abacavir is converted by cellular enzymes to the active metabolite, carbovir triphosphate (CBV-TP), an analogue of deoxyguanosine-5′-triphosphate (dGTP). CBV-TP inhibits the activity of HIV-1 reverse transcriptase (RT) both by competing with the natural substrate dGTP and by its incorporation into viral DNA.

Antiviral Activity

The antiviral activity of abacavir against HIV‑1 was assessed in a number of cell lines including primary monocytes/macrophages and peripheral blood mononuclear cells (PBMCs). EC50 values ranged from 3.7 to 5.8 microM (1 microM = 0.28 mcg per mL) and 0.07 to 1.0 microM against HIV‑1IIIB and HIV‑1BaL, respectively, and the mean EC50 value was 0.26 ± 0.18 microM against 8 clinical isolates. The median EC50 values of abacavir were 344 nM (range: 14.8 to 676 nM), 16.9 nM (range: 5.9 to 27.9 nM), 8.1 nM (range: 1.5 to 16.7 nM), 356 nM (range: 35.7 to 396 nM), 105 nM (range: 28.1 to 168 nM), 47.6 nM (range: 5.2 to 200 nM), 51.4 nM (range: 7.1 to 177 nM), and 282 nM (range: 22.4 to 598 nM) against HIV‑1 clades A-G and group O viruses (n = 3 except n = 2 for clade B), respectively. The EC50 values against HIV‑2 isolates (n = 4), ranged from 0.024 to 0.49 microM. The antiviral activity of abacavir in cell culture was not antagonized when combined with the nucleoside reverse transcriptase inhibitors (NRTIs) didanosine, emtricitabine, lamivudine, stavudine, tenofovir, zalcitabine or zidovudine, the non‑nucleoside reverse transcriptase inhibitor (NNRTI) nevirapine, or the protease inhibitor (PI) amprenavir. Ribavirin (50 microM) used in the treatment of chronic HCV infection had no effect on the anti–HIV‑1 activity of abacavir in cell culture.

Resistance

HIV‑1 isolates with reduced susceptibility to abacavir have been selected in cell culture. Genotypic analysis of isolates selected in cell culture and recovered from abacavir‑treated subjects demonstrated that amino acid substitutions K65R, L74V, Y115F, and M184V/I emerged in HIV-1 RT. M184V or I substitutions resulted in an approximately 2-fold decrease in susceptibility to abacavir. Substitutions K65R, L74M, or Y115F with M184V or I conferred a 7- to 8-fold reduction in abacavir susceptibility, and combinations of three substitutions were required to confer more than an 8-fold reduction in susceptibility.

Thirty‑nine percent (7 of 18) of the isolates from subjects who experienced virologic failure in the abacavir once‑daily arm had a greater than 2.5‑fold mean decrease in abacavir susceptibility with a median‑fold decrease of 1.3 (range: 0.5 to 11) compared with 29% (5 of 17) of the failure isolates in the twice‑daily arm with a median‑fold decrease of 0.92 (range: 0.7 to 13).

Cross-Resistance

Cross‑resistance has been observed among NRTIs. Isolates containing abacavir resistance‑associated substitutions, namely, K65R, L74V, Y115F, and M184V, exhibited cross‑resistance to didanosine, emtricitabine, lamivudine, and tenofovir in cell culture and in subjects. An increasing number of thymidine analogue mutation substitutions (TAMs: M41L, D67N, K70R, L210W, T215Y/F, K219E/R/H/Q/N) is associated with a progressive reduction in abacavir susceptibility.

13 NONCLINICAL TOXICOLOGY

13.1 Carcinogenesis, Mutagenesis, Impairment of Fertility

Carcinogenicity

Abacavir was administered orally at 3 dosage levels to separate groups of mice and rats in 2‑year carcinogenicity studies. Results showed an increase in the incidence of malignant and non‑malignant tumors. Malignant tumors occurred in the preputial gland of males and the clitoral gland of females of both species, and in the liver of female rats. In addition, non‑malignant tumors also occurred in the liver and thyroid gland of female rats. These observations were made at systemic exposures in the range of 6 to 32 times the human exposure at the recommended dose of 600 mg.

Mutagenicity

Abacavir induced chromosomal aberrations both in the presence and absence of metabolic activation in an in vitro cytogenetic study in human lymphocytes. Abacavir was mutagenic in the absence of metabolic activation, although it was not mutagenic in the presence of metabolic activation in an L5178Y mouse lymphoma assay. Abacavir was clastogenic in males and not clastogenic in females in an in vivo mouse bone marrow micronucleus assay.

Abacavir was not mutagenic in bacterial mutagenicity assays in the presence and absence of metabolic activation.

Impairment of Fertility

Abacavir did not affect male or female fertility in rats at a dose associated with exposures (AUC) approximately 3.3 times (male) or 4.1 times (female) those in humans at the clinically recommended dose.

13.2 Animal Toxicology and/or Pharmacology

Myocardial degeneration was found in mice and rats following administration of abacavir for 2 years. The systemic exposures were equivalent to 7 to 24 times the expected systemic exposure in humans at a dose of 600 mg. The clinical relevance of this finding has not been determined.

14 CLINICAL STUDIES

14.1 Adult Trials

Therapy-Naive Adults

CNA30024 was a multicenter, double-blind, controlled trial in which 649 HIV-1–infected, therapy-naive adults were randomized and received either ZIAGEN (300 mg twice daily), lamivudine (150 mg twice daily), and efavirenz (600 mg once daily); or zidovudine (300 mg twice daily), lamivudine (150 mg twice daily), and efavirenz (600 mg once daily). The duration of double-blind treatment was at least 48 weeks. Trial participants were male (81%), white (51%), black (21%), and Hispanic (26%). The median age was 35 years; the median pretreatment CD4+ cell count was 264 cells per mm^3, and median plasma HIV-1 RNA was 4.79 log10 copies per mL. The outcomes of randomized treatment are provided in Table 7.

Table 7. Outcomes of Randomized Treatment through Week 48 (CNA30024)
Outcome | ZIAGEN plus Lamivudine plus Efavirenz; (n = 324) | Zidovudine plus Lamivudine plus Efavirenz; (n = 325)
Respondera | 69% (73%) | 69% (71%)
Virologic failuresb | 6% | 4%
Discontinued due to adverse reactions | 14% | 16%
Discontinued due to other reasonsc | 10% | 11%
a Subjects achieved and maintained confirmed HIV-1 RNA less than or equal to 50 copies per mL (less than 400 copies per mL) through Week 48 (Roche AMPLICOR Ultrasensitive HIV-1 MONITOR standard test 1.0 PCR).
b Includes viral rebound, insufficient viral response according to the investigator, and failure to achieve confirmed less than or equal to 50 copies per mL by Week 48.
c Includes consent withdrawn, lost to follow up, protocol violations, those with missing data, clinical progression, and other.

After 48 weeks of therapy, the median CD4+ cell count increases from baseline were 209 cells per mm^3 in the group receiving ZIAGEN and 155 cells per mm^3 in the zidovudine group. Through Week 48, 8 subjects (2%) in the group receiving ZIAGEN (5 CDC classification C events and 3 deaths) and 5 subjects (2%) on the zidovudine arm (3 CDC classification C events and 2 deaths) experienced clinical disease progression.

CNA3005 was a multicenter, double-blind, controlled trial in which 562 HIV-1–infected, therapy-naive adults were randomized to receive either ZIAGEN (300 mg twice daily) plus COMBIVIR (lamivudine 150 mg/zidovudine 300 mg twice daily), or indinavir (800 mg 3 times a day) plus COMBIVIR twice daily. The trial was stratified at randomization by pre-entry plasma HIV-1 RNA 10,000 to 100,000 copies per mL and plasma HIV-1 RNA greater than 100,000 copies per mL. Trial participants were male (87%), white (73%), black (15%), and Hispanic (9%). At baseline the median age was 36 years; the median baseline CD4+ cell count was 360 cells per mm^3, and median baseline plasma HIV-1 RNA was 4.8 log10 copies per mL. Proportions of subjects with plasma HIV-1 RNA less than 400 copies per mL (using Roche AMPLICOR HIV-1 MONITOR Test) through 48 weeks of treatment are summarized in Table 8.

Table 8. Outcomes of Randomized Treatment through Week 48 (CNA3005)
Outcome | ZIAGEN plus Lamivudine/Zidovudine; (n = 262) | Indinavir plus Lamivudine/Zidovudine; (n = 265)
Respondera | 49% | 50%
Virologic failureb | 31% | 28%
Discontinued due to adverse reactions | 10% | 12%
Discontinued due to other reasonsc | 11% | 10%
a Subjects achieved and maintained confirmed HIV-1 RNA less than 400 copies per mL.
b Includes viral rebound and failure to achieve confirmed less than 400 copies per mL by Week 48.
c Includes consent withdrawn, lost to follow up, protocol violations, those with missing data, clinical progression, and other.

Treatment response by plasma HIV-1 RNA strata is shown in Table 9.

Table 9. Proportions of Responders through Week 48 by Screening Plasma HIV-1 RNA Levels (CNA3005)
Screening; HIV-1 RNA; (copies/mL) | ZIAGEN plus Lamivudine/Zidovudine; (n = 262) |  | Indinavir plus Lamivudine/Zidovudine; (n = 265)
Screening; HIV-1 RNA; (copies/mL) | <400 copies/mL | n | <400 copies/mL | n
≥10,000 - ≤100,000 | 50% | 166 | 48% | 165
>100,000 | 48% | 96 | 52% | 100

In subjects with baseline viral load greater than 100,000 copies per mL, percentages of subjects with HIV-1 RNA levels less than 50 copies per mL were 31% in the group receiving abacavir versus 45% in the group receiving indinavir.

Through Week 48, an overall mean increase in CD4+ cell count of about 150 cells per mm^3 was observed in both treatment arms. Through Week 48, 9 subjects (3.4%) in the group receiving abacavir (6 CDC classification C events and 3 deaths) and 3 subjects (1.5%) in the group receiving indinavir (2 CDC classification C events and 1 death) experienced clinical disease progression.

CNA30021 was an international, multicenter, double-blind, controlled trial in which 770 HIV-1–infected, therapy-naive adults were randomized and received either abacavir 600 mg once daily or abacavir 300 mg twice daily, both in combination with lamivudine 300 mg once daily and efavirenz 600 mg once daily. The double-blind treatment duration was at least 48 weeks. Trial participants had a mean age of 37 years; were male (81%), white (54%), black (27%), and American Hispanic (15%). The median baseline CD4+ cell count was 262 cells per mm^3 (range: 21 to 918 cells per mm^3) and the median baseline plasma HIV-1 RNA was 4.89 log10 copies per mL (range: 2.60 to 6.99 log10 copies per mL).

The outcomes of randomized treatment are provided in Table 10.

Table 10. Outcomes of Randomized Treatment through Week 48 (CNA30021)
Outcome | ZIAGEN 600 mg q.d. plus EPIVIR plus Efavirenz; (n = 384) | ZIAGEN 300 mg b.i.d. plus EPIVIR plus Efavirenz; (n = 386)
Respondera | 64% (71%) | 65% (72%)
Virologic failureb | 11% (5%) | 11% (5%)
Discontinued due to adverse reactions | 13% | 11%
Discontinued due to other reasonsc | 11% | 13%
a Subjects achieved and maintained confirmed HIV-1 RNA less than 50 copies per mL (less than 400 copies per mL) through Week 48 (Roche AMPLICOR Ultrasensitive HIV-1 MONITOR standard test version 1.0).
b Includes viral rebound, failure to achieve confirmed less than 50 copies per mL (less than 400 copies per mL) by Week 48, and insufficient viral load response.
c Includes consent withdrawn, lost to follow up, protocol violations, clinical progression, and other.

After 48 weeks of therapy, the median CD4+ cell count increases from baseline were 188 cells per mm^3 in the group receiving abacavir 600 mg once daily and 200 cells per mm^3 in the group receiving abacavir 300 mg twice daily. Through Week 48, 6 subjects (2%) in the group receiving ZIAGEN 600 mg once daily (4 CDC classification C events and 2 deaths) and 10 subjects (3%) in the group receiving ZIAGEN 300 mg twice daily (7 CDC classification C events and 3 deaths) experienced clinical disease progression. None of the deaths were attributed to trial medications.

14.2 Pediatric Trials

Therapy-Experienced Pediatric Subjects

CNA3006 was a randomized, double-blind trial comparing ZIAGEN 8 mg per kg twice daily plus lamivudine 4 mg per kg twice daily plus zidovudine 180 mg per m^2 twice daily versus lamivudine 4 mg per kg twice daily plus zidovudine 180 mg per m^2 twice daily. Two hundred and five therapy-experienced pediatric subjects were enrolled: female (56%), white (17%), black (50%), Hispanic (30%), median age of 5.4 years, baseline CD4+ cell percent greater than 15% (median = 27%), and median baseline plasma HIV-1 RNA of 4.6 log10 copies per mL. Eighty percent and 55% of subjects had prior therapy with zidovudine and lamivudine, respectively, most often in combination. The median duration of prior nucleoside analogue therapy was 2 years. At 16 weeks, the proportion of subjects responding based on plasma HIV-1 RNA less than or equal to 400 copies per mL was significantly higher in subjects receiving ZIAGEN plus lamivudine plus zidovudine compared with subjects receiving lamivudine plus zidovudine, 13% versus 2%, respectively. Median plasma HIV-1 RNA changes from baseline were -0.53 log10 copies per mL in the group receiving ZIAGEN plus lamivudine plus zidovudine compared with -0.21 log10 copies per mL in the group receiving lamivudine plus zidovudine. Median CD4+ cell count increases from baseline were 69 cells per mm^3 in the group receiving ZIAGEN plus lamivudine plus zidovudine and 9 cells per mm^3 in the group receiving lamivudine plus zidovudine.

Once-Daily Dosing

ARROW (COL105677) was a 5-year randomized, multicenter trial which evaluated multiple aspects of clinical management of HIV-1 infection in pediatric subjects. HIV-1–infected, treatment-naive subjects aged 3 months to 17 years were enrolled and treated with a first-line regimen containing ZIAGEN and lamivudine, dosed twice daily according to World Health Organization recommendations. After a minimum of 36 weeks of treatment, subjects were given the option to participate in Randomization 3 of the ARROW trial, comparing the safety and efficacy of once-daily dosing with twice-daily dosing of ZIAGEN and lamivudine, in combination with a third antiretroviral drug, for an additional 96 weeks. Of the 1,206 original ARROW subjects, 669 participated in Randomization 3. Virologic suppression was not a requirement for participation at baseline for Randomization 3 (following a minimum of 36 weeks of twice-daily treatment), 75% of subjects in the twice-daily cohort were virologically suppressed compared with 71% of subjects in the once-daily cohort.

The proportions of subjects with HIV-1 RNA less than 80 copies per mL through 96 weeks are shown in Table 11. The differences between virologic responses in the two treatment arms were comparable across baseline characteristics for gender and age.

Table 11. Virologic Outcome of Randomized Treatment at Week 96a (ARROW Randomization 3)
Outcome | ZIAGEN plus Lamivudine Twice-Daily Dosing; (n = 333) | ZIAGEN plus Lamivudine Once-Daily Dosing; (n = 336)
HIV-1 RNA <80 copies/mLb | 70% | 67%
HIV-1 RNA ≥80 copies/mLc | 28% | 31%
No virologic data
Discontinued due to adverse event or death | 1% | <1%
Discontinued study for other reasonsd | 0% | <1%
Missing data during window but on study | 1% | 1%
a Analyses were based on the last observed viral load data within the Week 96 window.
b Predicted difference (95% CI) of response rate is -4.5% (-11% to 2%) at Week 96.
c Includes subjects who discontinued due to lack or loss of efficacy or for reasons other than an adverse event or death, and who had a viral load value of greater than or equal to 80 copies per mL, or subjects who had a switch in background regimen that was not permitted by the protocol.
d Other includes reasons such as withdrew consent, loss to follow-up, etc. and the last available HIV-1 RNA less than 80 copies per mL (or missing).

16 HOW SUPPLIED/STORAGE AND HANDLING

ZIAGEN tablets, containing abacavir sulfate equivalent to 300 mg abacavir are yellow, biconvex, scored, capsule-shaped, film-coated, and imprinted with “GX 623” on both sides. They are packaged as follows:

Bottles of 60 tablets (NDC 49702-221-18) with child-resistant closure.

Store at controlled room temperature of 20° to 25°C (68° to 77°F) (see USP).

ZIAGEN oral solution is a clear to opalescent, yellowish, strawberry-banana-flavored liquid, which may turn brown over time. Each mL of the solution contains abacavir sulfate equivalent to 20 mg of abacavir. It is packaged in plastic bottles as follows:

Bottles of 240 mL (NDC 49702-222-48) with child-resistant closure. This product does not require reconstitution.

Store at controlled room temperature of 20° to 25°C (68° to 77°F) (see USP). DO NOT FREEZE. May be refrigerated.

17 PATIENT COUNSELING INFORMATION

Advise the patient to read the FDA-approved patient labeling (Medication Guide).

Hypersensitivity Reactions

Inform patients:

- that a Medication Guide and Warning Card summarizing the symptoms of the abacavir hypersensitivity reaction and other product information will be dispensed by the pharmacist with each new prescription and refill of ZIAGEN and instruct the patient to read the Medication Guide and Warning Card every time to obtain any new information that may be present about ZIAGEN. The complete text of the Medication Guide is reprinted at the end of this document.
- to carry the Warning Card with them.
- how to identify a hypersensitivity reaction [see Warnings and Precautions (5.1), Medication Guide].
- that if they develop symptoms consistent with a hypersensitivity reaction they should call their healthcare provider right away to determine if they should stop taking ZIAGEN.
- that a hypersensitivity reaction can worsen and lead to hospitalization or death if ZIAGEN is not immediately discontinued.
- to not restart ZIAGEN or any other abacavir‑containing product following a hypersensitivity reaction because more severe symptoms can occur within hours and may include life‑threatening hypotension and death.
- that if they have a hypersensitivity reaction, they should dispose of any unused ZIAGEN to avoid restarting abacavir.
- that a hypersensitivity reaction is usually reversible if it is detected promptly and ZIAGEN is stopped right away.
- that if they have interrupted ZIAGEN for reasons other than symptoms of hypersensitivity (for example, those who have an interruption in drug supply), a serious or fatal hypersensitivity reaction may occur with reintroduction of abacavir.
- to not restart ZIAGEN or any other abacavir‑containing product without medical consultation and only if medical care can be readily accessed by the patient or others.

Lactic Acidosis/Hepatomegaly with Steatosis

Advise patients that lactic acidosis and severe hepatomegaly with steatosis have been reported with use of nucleoside analogues and other antiretrovirals. Advise patients to stop taking ZIAGEN if they develop clinical symptoms suggestive of lactic acidosis or pronounced hepatotoxicity [see Warnings and Precautions (5.2)].

Immune Reconstitution Syndrome

Advise patients to inform their healthcare provider immediately of any signs and symptoms of infection as inflammation from previous infection may occur soon after combination antiretroviral therapy, including when ZIAGEN is started [see Warnings and Precautions (5.3)].

Pregnancy Registry

Advise patients that there is a pregnancy exposure registry that monitors pregnancy outcomes in women exposed to ZIAGEN during pregnancy [see Use in Specific Populations (8.1)].

Lactation

Instruct women with HIV-1 infection not to breastfeed because HIV-1 can be passed to the baby in the breast milk [see Use in Specific Populations (8.2)].

Missed Dose

Instruct patients that if they miss a dose of ZIAGEN, to take it as soon as they remember. Advise patients not to double their next dose or take more than the prescribed dose [see Dosage and Administration (2)].

Availability of Medication Guide

Instruct patients to read the Medication Guide before starting ZIAGEN and to re-read it each time the prescription is renewed. Instruct patients to inform their physician or pharmacist if they develop any unusual symptom, or if any known symptom persists or worsens.

COMBIVIR, EPIVIR, and ZIAGEN are trademarks owned by or licensed to the ViiV Healthcare group of companies.

The other brands listed are owned by or licensed to their respective owner and are not owned by or licensed to the ViiV Healthcare group of companies. The makers of these brands are not affiliated with and do not endorse the ViiV Healthcare group of companies or its products.

Manufactured for:

ViiV Healthcare

Durham, NC 27701

©2023 ViiV Healthcare group of companies or its licensor.

ZGN:16PI

MEDICATION GUIDE

ZIAGEN (ZY-uh-jen) ZIAGEN (ZY-uh-jen)

(abacavir) (abacavir)

tablets oral solution

What is the most important information I should know about ZIAGEN?

ZIAGEN can cause serious side effects, including:

- Serious allergic reactions (hypersensitivity reaction) that can cause death have happened with ZIAGEN and other abacavir-containing products. Your risk of this allergic reaction is much higher if you have a gene variation called HLA‑B*5701. Your healthcare provider can determine with a blood test if you have this gene variation.
If you get a symptom from 2 or more of the following groups while taking ZIAGEN, call your healthcare provider right away to find out if you should stop taking ZIAGEN.
Symptom(s)
Group 1 Fever
Group 2 Rash
Group 3 Nausea, vomiting, diarrhea, abdominal (stomach area) pain
Group 4 Generally ill feeling, extreme tiredness, or achiness
Group 5 Shortness of breath, cough, sore throat

A list of these symptoms is on the Warning Card your pharmacist gives you. Carry this Warning Card with you at all times.

If you stop ZIAGEN because of an allergic reaction, never take ZIAGEN (abacavir) or any other abacavir‑containing medicine (EPZICOM, TRIUMEQ, or TRIZIVIR) again.

- If you have an allergic reaction, dispose of any unused ZIAGEN. Ask your pharmacist how to properly dispose of medicines.
- If you take ZIAGEN or any other abacavir-containing medicine again after you have had an allergic reaction, within hours you may get life-threatening symptoms that may include very low blood pressure or death.
- If you stop ZIAGEN for any other reason, even for a few days, and you are not allergic to ZIAGEN, talk with your healthcare provider before taking it again. Taking ZIAGEN again can cause a serious allergic or life‑threatening reaction, even if you never had an allergic reaction to it before.

If your healthcare provider tells you that you can take ZIAGEN again, start taking it when you are around medical help or people who can call a healthcare provider if you need one.

What is ZIAGEN?

ZIAGEN is a prescription HIV-1 (Human Immunodeficiency Virus type 1) medicine used with other antiretroviral medicines to treat HIV-1 infection. HIV-1 is the virus that causes Acquired Immune Deficiency Syndrome (AIDS).

The safety and effectiveness of ZIAGEN has not been established in children under 3 months of age.

When used with other antiretroviral medicines to treat HIV-1 infection, ZIAGEN may help:

- reduce the amount of HIV-1 in your blood. This is called “viral load”.
- increase the number of CD4+ (T) cells in your blood, that help fight off other infections.

Reducing the amount of HIV-1 and increasing the CD4+ (T) cells in your blood may help improve your immune system. This may reduce your risk of death or getting infections that can happen when your immune system is weak (opportunistic infections).

ZIAGEN does not cure HIV-1 infection or AIDS. You must keep taking HIV-1 medicines to control HIV-1 infection and decrease HIV-related illnesses.

Who should not take ZIAGEN?

Do not take ZIAGEN if you:

- have a certain type of gene variation called the HLA‑B*5701 allele. Your healthcare provider will test you for this before prescribing treatment with ZIAGEN.
- are allergic to abacavir or any of the ingredients in ZIAGEN. See the end of this Medication Guide for a complete list of ingredients in ZIAGEN.
- have liver problems.

What should I tell my healthcare provider before taking ZIAGEN?

Before you take ZIAGEN, tell your healthcare provider if you:

- have been tested and know whether or not you have a particular gene variation called HLA‑B*5701.
- have or have had liver problems, including hepatitis B or C virus infection.
- have heart problems, smoke, or have diseases that increase your risk of heart disease such as high blood pressure, high cholesterol, or diabetes.
- drink alcohol or take medicines that contain alcohol.
- are pregnant or plan to become pregnant. Talk to your healthcare provider if you are pregnant or plan to become pregnant.
  Pregnancy Registry. There is a pregnancy registry for women who take antiretroviral medicines during pregnancy. The purpose of this registry is to collect information about the health of you and your baby. Talk to your healthcare provider about how you can take part in this registry.
- are breastfeeding or plan to breastfeed. Do not breastfeed if you take ZIAGEN.
- You should not breastfeed if you have HIV-1 because of the risk of passing HIV-1 to your baby.

Tell your healthcare provider about all the medicines you take, including prescription and over-the-counter medicines, vitamins, and herbal supplements.

Some medicines interact with ZIAGEN. Keep a list of your medicines to show your healthcare provider and pharmacist. You can ask your healthcare provider or pharmacist for a list of medicines that interact with ZIAGEN. Do not start taking a new medicine without telling your healthcare provider. Your healthcare provider can tell you if it is safe to take ZIAGEN with other medicines.

Tell your healthcare provider if you take:

- any other medicine to treat HIV-1
- methadone
- riociguat

How should I take ZIAGEN?

- Take ZIAGEN exactly as your healthcare provider tells you.
- Do not change your dose or stop taking ZIAGEN without talking with your healthcare provider. If you miss a dose of ZIAGEN, take it as soon as you remember. Do not take 2 doses at the same time. If you are not sure about your dosing, call your healthcare provider.
- Stay under the care of a healthcare provider while taking ZIAGEN.
- ZIAGEN may be taken with or without food.
- For children aged 3 months and older, your healthcare provider will prescribe a dose of ZIAGEN based on your child’s body weight.
- Tell your healthcare provider if you or your child has trouble swallowing tablets. ZIAGEN comes as a tablet or as a liquid (oral solution).
- Do not run out of ZIAGEN. The virus in your blood may increase and the virus may become harder to treat. When your supply starts to run out, get more from your healthcare provider or pharmacy.
- If you take too much ZIAGEN, call your healthcare provider or go to the nearest hospital emergency room right away.

What are the possible side effects of ZIAGEN?

- ZIAGEN can cause serious side effects including:
- See “What is the most important information I should know about ZIAGEN?”
- Build-up of acid in your blood (lactic acidosis). Lactic acidosis can happen in some people who take ZIAGEN. Lactic acidosis is a serious medical emergency that can cause death. Call your healthcare provider right away if you get any of the following symptoms that could be signs of lactic acidosis:

○feel very weak or tired
○unusual (not normal) muscle pain
○trouble breathing
○stomach pain with nausea and vomiting

○feel cold, especially in your arms and legs
○feel dizzy or light-headed
○have a fast or irregular heartbeat

- Serious liver problems can happen in people who take ZIAGEN. In some cases, these serious liver problems can lead to death. Your liver may become large (hepatomegaly) and you may develop fat in your liver (steatosis) when you take ZIAGEN. Call your healthcare provider right away if you have any of the following signs of liver problems:

○your skin or the white part of your eyes turns yellow (jaundice)
○dark or “tea-colored” urine
○light-colored stools (bowel movements)

○loss of appetite for several days or longer
○nausea
○pain, aching, or tenderness on the right side of your stomach area

You may be more likely to get lactic acidosis or serious liver problems if you are female or very overweight (obese).

- Changes in your immune system (Immune Reconstitution Syndrome) can happen when you start taking HIV-1 medicines. Your immune system may get stronger and begin to fight infections that have been hidden in your body for a long time. Tell your healthcare provider right away if you start having new symptoms after you start taking ZIAGEN.
- Heart attack (myocardial infarction). Some HIV-1 medicines including ZIAGEN may increase your risk of heart attack.

The most common side effects of ZIAGEN in adults include:

• nausea • tiredness

• headache • vomiting

• generally not feeling well • bad dreams or sleep problems

The most common side effects of ZIAGEN in children include:

• fever and chills • rash

• nausea • ear, nose, or throat infections

Tell your healthcare provider if you have any side effect that bothers you or that does not go away.

These are not all the possible side effects of ZIAGEN. For more information, ask your healthcare provider or pharmacist. Call your doctor for medical advice about side effects. You may report side effects to FDA at 1‑800‑FDA‑1088.

How should I store ZIAGEN?

- Store ZIAGEN at room temperature, between 68°F to 77°F (20°C to 25°C).
- Do not freeze ZIAGEN oral solution. You may store ZIAGEN oral solution in a refrigerator.

Keep ZIAGEN and all medicines out of the reach of children.

General information for safe and effective use of ZIAGEN

Medicines are sometimes prescribed for purposes other than those listed in a Medication Guide. Do not use ZIAGEN for a condition for which it was not prescribed. Do not give ZIAGEN to other people, even if they have the same symptoms that you have. It may harm them.

If you would like more information, talk with your healthcare provider. You can ask your healthcare provider or pharmacist for the information about ZIAGEN that is written for health professionals.

For more information go to www.ZIAGEN.com or call 1-877-844-8872.

What are the ingredients in ZIAGEN?

Active ingredient: abacavir

Inactive ingredients:

Tablets:

Colloidal silicon dioxide, magnesium stearate, microcrystalline cellulose, and sodium starch glycolate.

Tablet film‑coating contains: hypromellose, polysorbate 80, synthetic yellow iron oxide, titanium dioxide, and triacetin.

Oral Solution:

Artificial strawberry and banana flavors, citric acid (anhydrous), methylparaben and propylparaben (added as preservatives), propylene glycol, saccharin sodium, sodium citrate (dihydrate), sorbitol solution, and water.

Manufactured for:
ViiV Healthcare
Durham, NC 27701

EPZICOM, TRIUMEQ, TRIZIVIR, and ZIAGEN are trademarks owned by or licensed to the ViiV Healthcare group of companies.

©2023 ViiV Healthcare group of companies or its licensor.

ZGN:12MG

This Medication Guide has been approved by the U.S. Food and Drug Administration.

Revised: 7/2023

PACKAGE LABEL

PRINCIPAL DISPLAY PANEL

NDC 49702-222-48

ZIAGEN

(abacavir)

ORAL SOLUTION

20 mg/mL

Each mL contains abacavir sulfate equivalent to 20 mg of abacavir.

Rx only

Notice to Authorized Dispenser:

Each time ZIAGEN is dispensed, give the patient a Medication Guide and Warning Card from the carton.

240 mL

Made in Canada

Trademarks are owned by or licensed to the ViiV Healthcare group of companies.

©2023 the ViiV Healthcare group of companies

30000000001069 Rev. 8/23